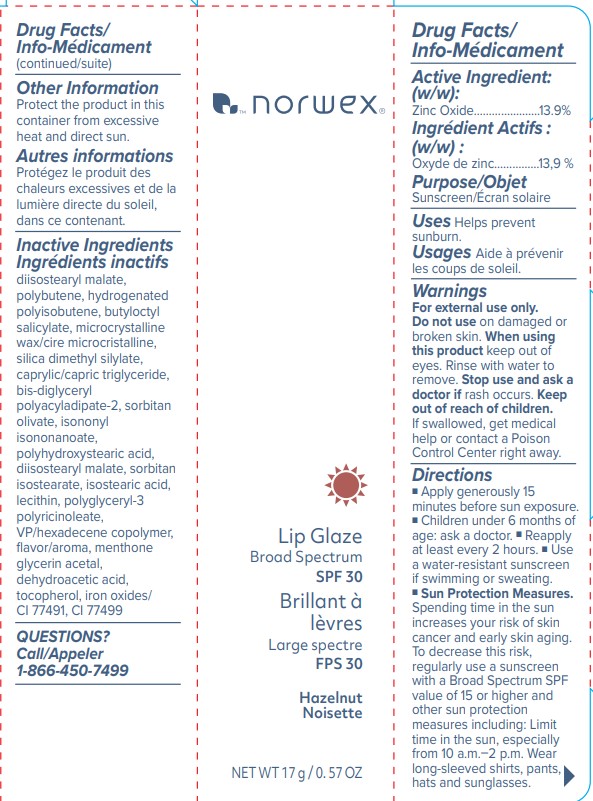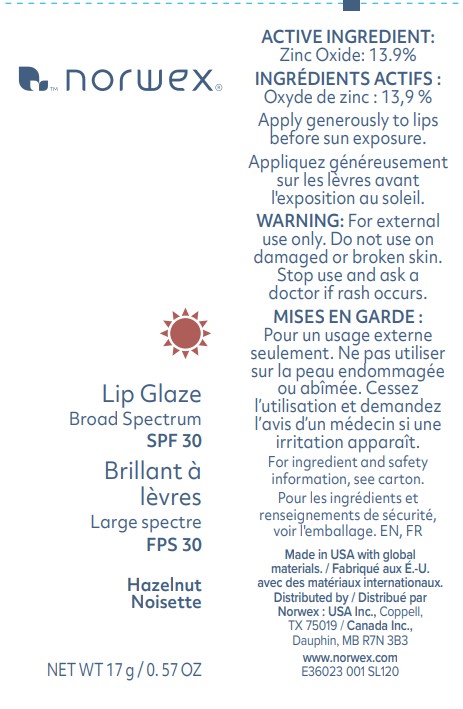 DRUG LABEL: Norwex Lip Glaze Broad Spectrum SPF 30
NDC: 80971-103 | Form: LIPSTICK
Manufacturer: Norwex Usa, Inc.
Category: otc | Type: HUMAN OTC DRUG LABEL
Date: 20251120

ACTIVE INGREDIENTS: ZINC OXIDE 139 mg/1 g
INACTIVE INGREDIENTS: DIISOSTEARYL MALATE; BUTYLOCTYL SALICYLATE; MICROCRYSTALLINE WAX; SILICA DIMETHYL SILYLATE; CAPRYLIC/CAPRIC TRIGLYCERIDE; BIS-DIGLYCERYL POLYACYLADIPATE-2; SORBITAN OLIVATE; ISONONYL ISONONANOATE; SORBITAN ISOSTEARATE; ISOSTEARIC ACID; VP/HEXADECENE COPOLYMER; MENTHONE GLYCERIN ACETAL; DEHYDROACETIC ACID; TOCOPHEROL

Norwex Lip Glaze Broad Spectrum SPF 30

Active Ingredient

Zinc Oxide 13.9%

Purpose

Sunscreen

Uses

Helps prevent sunburn

Warnings

For external use only

Do not use

on damaged of broken skin

When using this product

keep out of eyes. Rinse with water to remove

Stop use and ask

a doctor if rash occurs

Keep out of reach of children

If product is swallowed, get medical help or contact a Poison Control Center right away.

Directions

- Apply generously 15 minutes before sun exposure
- Children under 6 months of age:ask a doctor.
- reapply at least every 2 hours
- use a water-resistant sunscreen if swimming or sweating
- Sun Protection Measures Spending time in the sun increases your risk of skin cancer and early skin aging. To decrease this risk, regularyly use a sunscreen with a Broad Spectrum value of SPF 15 or higher and other sun protection measures including
- Limit time in the sun, especially from 10 a.m.- 2 p.m.
- wear long-sleeved shiirts, pants, hats and sunglasses

Other Information

Protect the product in this container from excessive heat and direct sun

Inactive ingredients

Diisostearyl malate, polybutene, hydrogenated polyisobutene, butyloctyl salicylate, microcrystalline wax/cire microcristalline, silica dimethyl silylate, caprylic/capric triglyceride, bis-diglyceryl polyacyladipate-2, sorbitan olivate, isononyl isononanoate, polyhydroxystearic acid, sorbitan isostearate, isostearic acid, lecithin, polyglyceryl-3 polyricinoleate, VP/hexadecene copolymer, flavor/aroma, menthone glycerin acetal, dehydroacetic acid, tocopherol, iron oxides/CI 77491, CI 77499

Questions?

Call 1-866-450-7499